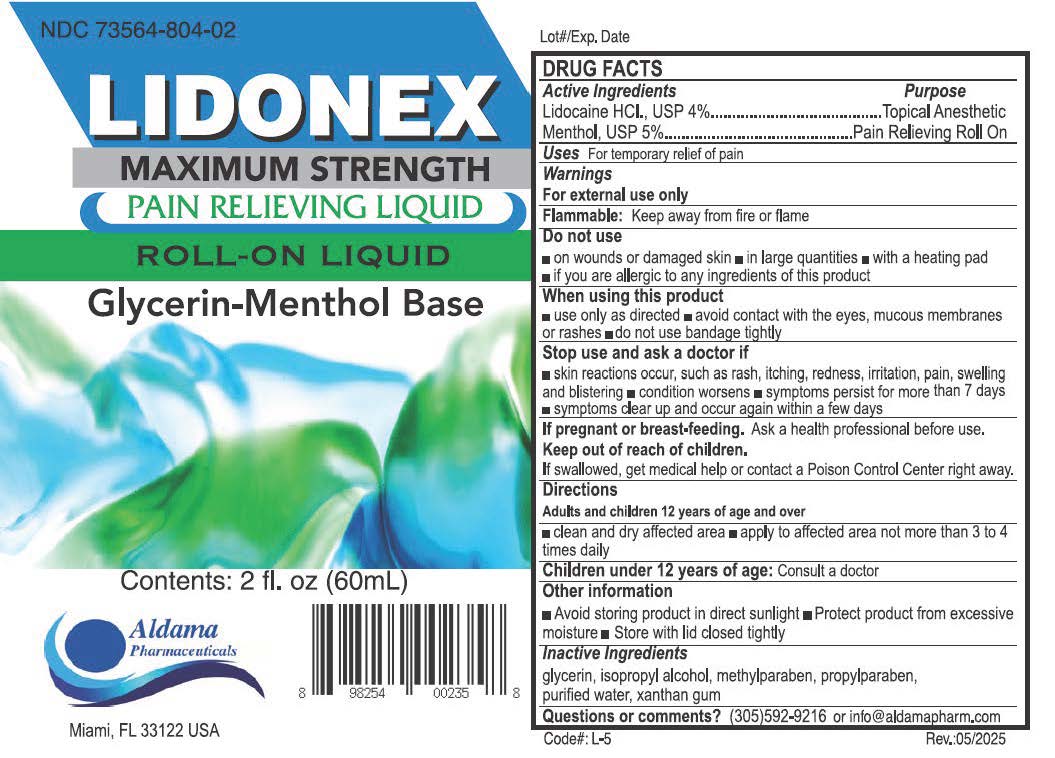 DRUG LABEL: Lidonex
NDC: 73564-804 | Form: LIQUID
Manufacturer: Aldama Pharmaceuticals, Inc
Category: otc | Type: HUMAN OTC DRUG LABEL
Date: 20251014

ACTIVE INGREDIENTS: MENTHOL 5 g/100 mL; LIDOCAINE HYDROCHLORIDE 4 g/100 mL
INACTIVE INGREDIENTS: GLYCERIN; ISOPROPYL ALCOHOL; METHYLPARABEN; PROPYLPARABEN; WATER; XANTHAN GUM

Lidonex Roll-On Liquid

Active Ingredient

Lidocaine HCL, USP 4%

Menthol USP 5%

Purpose

Topical Anesthetic

Pain Relieving

Use

For temporarily relief of pain

Warnings

For external use only

Flammable: Keep away from fire or flame

Do not use

- on wounds or damaged skin
- in large quantaties
- with a heating pad
- if you are allergic to any ingredients of this product

When using this product

- use only as directed.
- avoid contact with the eyes, mucous membranes or rashes
- do not bandage tightly

Stop use and ask doctor if

- skin reactions occur, such as rash, itching, redness, irritation, pain, swelling and blistering
- condition worsens
- symptoms persist for more than 7 days
- symptoms clear up and occur again within a few days

PREGNANCY OR BREAST FEEDING

If pregnant or breast-feeding.Ask a health professional before use.

Keep out of reach of children.If swallowed, get medical help or contact a Poison Control Center right away.

Directions

Adults and children over 12 years of age and over

- clean and dry affected area
- apply to affected area not more than 3 to 4 times daily

Children under 12 years of age:Consult a doctor

Inactive ingredients

glycerin, isopropyl alcohol, methylparaben, propylparaben, purified water, xanthan gum

STORAGE AND HANDLING

- avoid storing prouct in direct sunlight
- prodect product from excessive moisture
- store with lid closed tightly

Questions or comments?(305) 592 - 9216 or info@aldamapharm.com